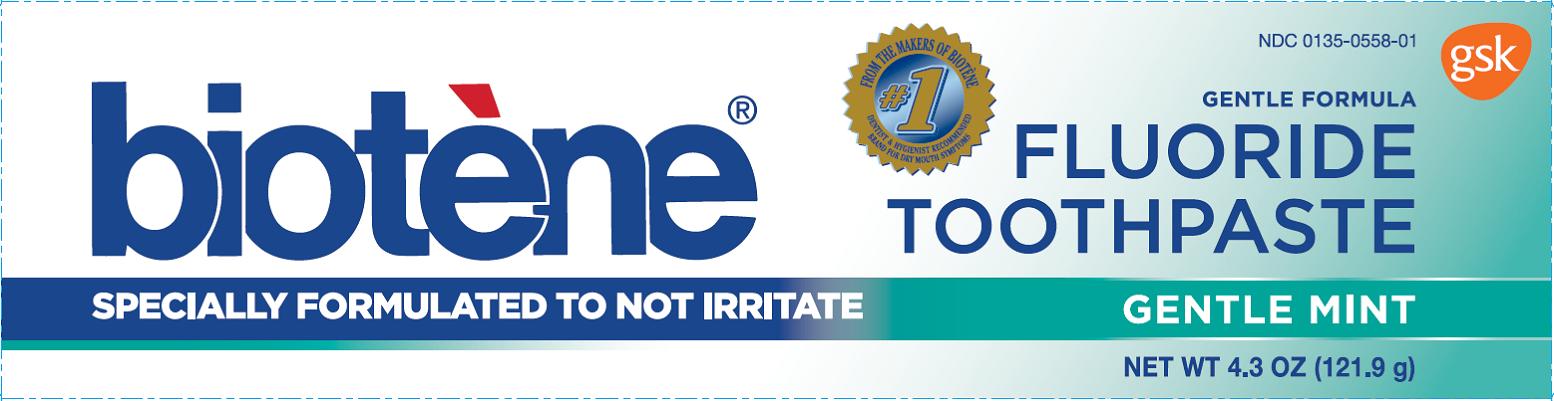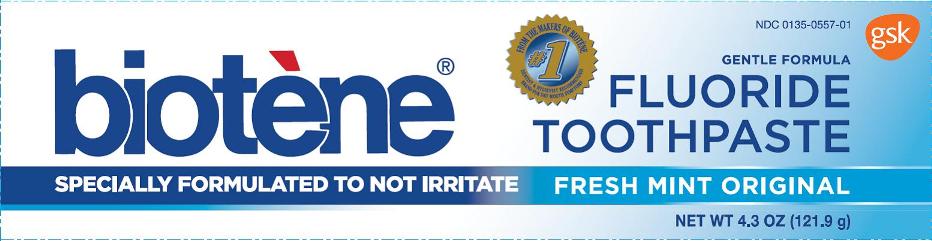 DRUG LABEL: BIOTENE
NDC: 0135-0557 | Form: PASTE
Manufacturer: Haleon US Holdings LLC
Category: otc | Type: HUMAN OTC DRUG LABEL
Date: 20241105

ACTIVE INGREDIENTS: SODIUM FLUORIDE 1.5 mg/1 g
INACTIVE INGREDIENTS: WATER; SORBITOL; HYDRATED SILICA; GLYCERIN; POLYETHYLENE GLYCOL 400; COCAMIDOPROPYL BETAINE; XANTHAN GUM; SACCHARIN SODIUM; SUCRALOSE; TITANIUM DIOXIDE; SODIUM HYDROXIDE

Drug Facts

Active ingredient

Sodium Fluoride (0.15% w/v fluoride ion)

Purpose

Anticavity

Use

aids in the prevention of dental cavities

Warnings

Keep out of reach of children 12 years of age and under (Fresh Mint and Gentle Mint)

If you accidentally swallow more than used for brushing, get medical help or contact a Poison Control Center right away. Do not use if you are allergic to any of the ingredients.

Keep out of reach of children 12 years of age and under. (PBF)

If you accidentally swallow more than used for brushing, get medical help or contact a Poison Control Center right away. If symptoms of a dry mouth persist, consult a healthcare professional. Do not use if you are allergic to any of the ingredients.

Directions

Adults and children over 12 years

- apply toothpaste onto a soft bristle toothbrush
- brush thoroughly after meals or at least twice a day or use as directed by a dentist or physician.

Children 12 years and under ask a dentist or physician. Once recommended, to minimize swallowing for children under 6, use a pea-sized amount and supervise brushing until good habits are established.

Other information

store below 25°C (77F°)

Inactive ingredients (Fresh Mint Original)

Water, Sorbitol, Hydrated Silica, Glycerin, PEG-8, Cocamidopropyl Betaine, Xanthan Gum, Flavor, Sodium Saccharin, Sucralose, Titanium Dioxide, Sodium Hydroxide

Inactive ingredients (Gentle Mint)

Water, Sorbitol, Hydrated Silica, Glycerin, PEG-8, Cocamidopropyl Betaine, Xanthan Gum, Flavor, Sodium Saccharin, Sucralose, Sodium Hydroxide, D&C Yellow #10, FD&C Blue #1

Questions or comments?

call toll-free 1-800-922-5856 weekdays

Principal Display Panel

NDC 0135-0557-01

biotene®

FLUORIDE TOOTHPASTE

GENTLE FORMULA

SPECIALLY FORMULATED TO NOT IRRITATE

FRESH MINT ORIGINAL

NET WT 4.3 OZ (121.9g)

FROM THE MAKERS OF BIOTENE

#1 DENTIST & HYGIENTIST RECOMMENDED BRAND FOR DRY MOUTH SYMPTOMS

HELPS MAINTAIN ORAL ENVIRONMENT

- HELPS FRESHEN BAD BREATH
- SLS FREE
- BALANCED PH
- GENTLE FORMULA
- ESSENTIAL FLUORIDE TOOTH PROTECTION

Also look for other biotene® products including biotene® Oral Rinses, biotene® oralbalance Gel, and biotene® Mouth Spray.

ALWAYS FOLLOW THE LABEL

This product contains no Sodium Lauryl Sulfate (SLS)

Biotene, oralbalance and graphic elements are trademarks of the GSK group of companies.

www.biotene.com

Distributed by:

GlaxoSmithKline

Consumer Healthcare, L.P.

Moon Township, PA 15108

©2014 GSK

102875XC

Principal Display Panel

NDC 0135-0558-01

biotene®

FLUORIDE TOOTHPASTE

GENTLE FORMULA

SPECIALLY FORMULATED TO NOT IRRITATE

GENTLE MINT

NET WT 4.3 OZ (121.9g)

FROM THE MAKERS OF BIOTENE

#1 DENTIST & HYGIENTIST RECOMMENDED BRAND FOR DRY MOUTH SYMPTOMS

HELPS MAINTAIN ORAL ENVIRONMENT

- HELPS FRESHEN BAD BREATH
- SLS FREE
- BALANCED PH
- GENTLE FORMULA
- ESSENTIAL FLUORIDE TOOTH PROTECTION

Also look for other biotene® products including biotene® Oral Rinses, biotene® oralbalance Gel, and biotene® Mouth Spray.

ALWAYS FOLLOW THE LABEL

This product contains no Sodium Lauryl Sulfate (SLS)

Biotene, oralbalance and graphic elements are trademarks of the GSK group of companies.

Distributed by:

GlaxoSmithKline

Consumer Healthcare, L.P.

Moon Township, PA 15108

©2014 GSK

102874XC